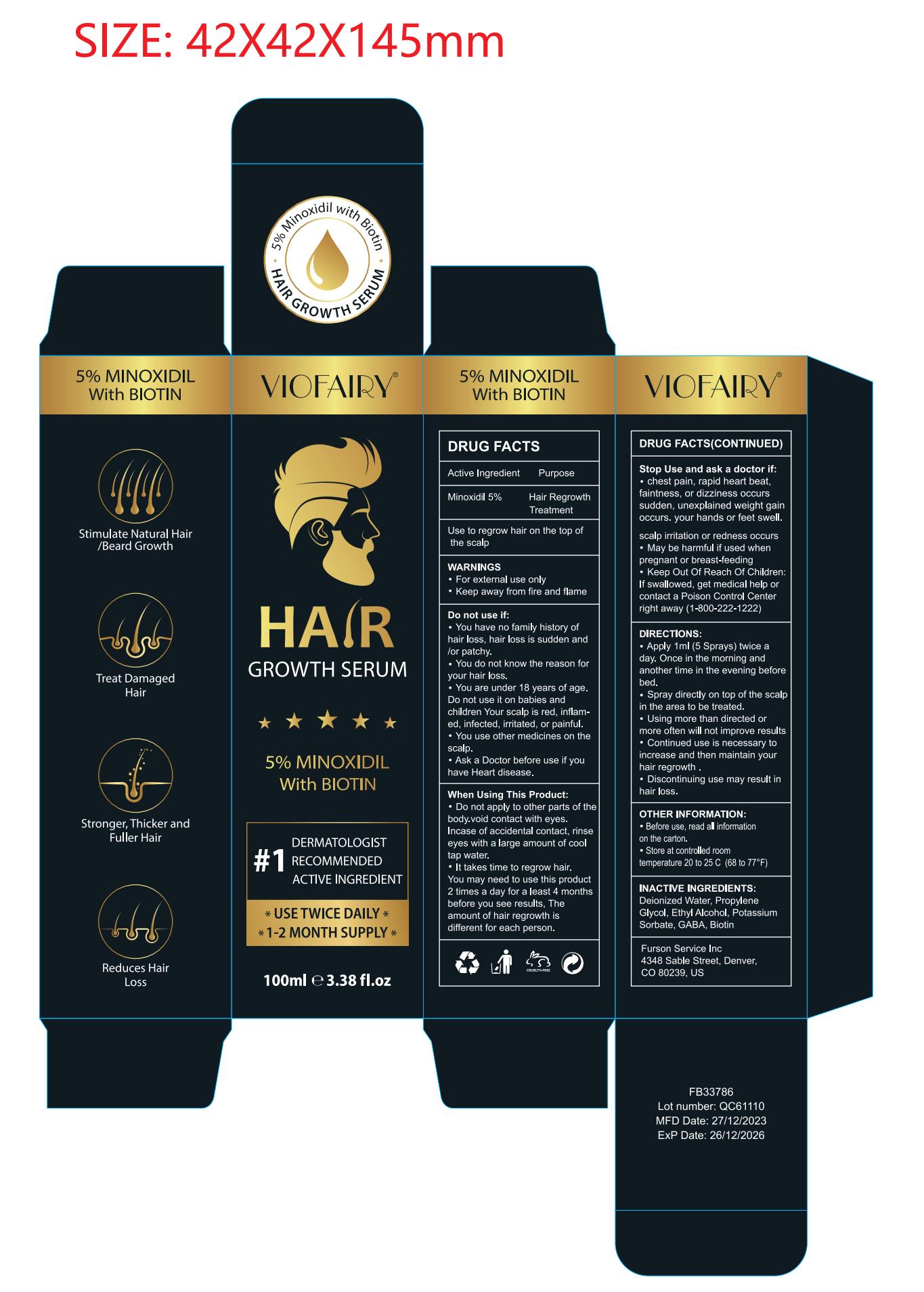 DRUG LABEL: VIOFAIRY 5% Minoxidil Spray.
NDC: 83804-105 | Form: LIQUID
Manufacturer: Shenzhen Shandian Jingling Technology Co., Ltd.
Category: otc | Type: HUMAN OTC DRUG LABEL
Date: 20240131

ACTIVE INGREDIENTS: MINOXIDIL 5 g/100 mL
INACTIVE INGREDIENTS: .GAMMA.-AMINOBUTYRIC ACID; ALCOHOL; POTASSIUM SORBATE; BIOTIN; WATER; PROPYLENE GLYCOL

83804-105

Active Ingredient

Minoxidil 5%

Purpose

Hair Regrowth Treatment

Use

to regrow hair on the top of the scalp

Warnings

For external use only

Keep away from fire and flam

Do not use

You have no family history of hair loss,hair loss is sudden and/or patchy

you are under 18 years of age.Do not use it on babies and children

When Using

Do not apply on other parts of the body

void contact with eyes. In case of accidental contact, rinse eyes with a large amount of cool tap water

It takes time to regrow hair. You may need to use this product 2 times a day for a least 4 months before you see results, The amount of hair regrowth is different for each person

Stop Use

chest pain, rapid heart beat, faintness, or dizziness occurs

sudden, unexplained weight gain occurs

your hands or feet swell

scalp irritation or redness occurs May be harmful if used when pregnant or breast-feeding
. Keep Out Of Reach Of Children:If swallowed, get medical help or contact a Poison Control Center right away.

Ask Doctor

When Pregnant or breast-feeding

Keep Oot Of Reach Of Children

If swallowed, get medical help or contact a Poison Control Center right away. (1-800-222-1222)

Directions

.Apply 1ml(5 Sprays) twice a day. Once in the morning and another time in the evening before bed
.Spray directly on top of the scalp in the area to be treated Using more than directed or more often will not improve results
. Continued use is necessary to increase and then maintain your hair regrowth .
. Discontinuing use may result in hair loss.

Other information

Before use, read all information on the carton

Store at controlled room temperature 20 to 25 C (68 to 77°F)

Inactive ingredients

biotin
Deionized Water
Propylene Glycol
Ethyl Alcohol
Potassium Sorbate
GABA

Questions

service@amazonfairy.com